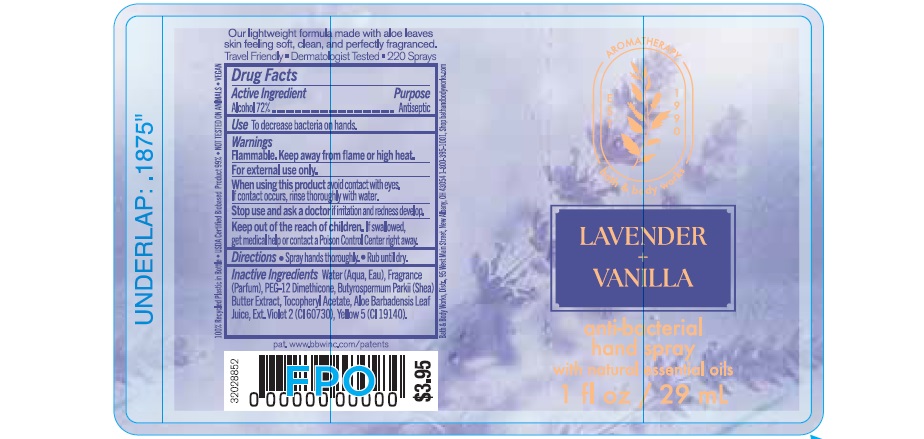 DRUG LABEL: Anti-BacterialHandSpray
NDC: 62670-6883 | Form: SPRAY
Manufacturer: Bath & Body Works, Inc.
Category: otc | Type: HUMAN OTC DRUG LABEL
Date: 20260302

ACTIVE INGREDIENTS: ALCOHOL 72 mL/100 mL
INACTIVE INGREDIENTS: WATER

1oz ABHS Lavender and Vanilla

Active Ingredient

Alcohol 72%

Purpose

Antiseptic

Use

Decreases bacteria on hands.

Warnings

Flammable. Keep away from flame or high heat.

WARNINGS

For external use only.

When using this product, avoid contact with eyes. If contact occurs, rinse thoroughly with water.

Stop use and ask a doctor if irritation and redness develop.

Keep out of reach of children. If swallowed, get medical help or contact a Poison Control Center right away.

Directions

- Spray hands thoroughly.
- Rub until dry.

INACTIVE INGREDIENT

Water (Aqua, Eau), Fragrance (Parfum), PEG-12 Dimethicone, Butyrospermum Parkii (Shea) Butter Extract, Tocopheryl Acetate, Aloe Barbadensis Leaf Juice, Ext. Violet 2 (CI 60730), Yellow 5 (CI 19140).

Bath & Body Works Distr., 95 West Main Street

New Albany, OH 43054, 1-800-395-1001

pat. www.bbwinc.com/patents